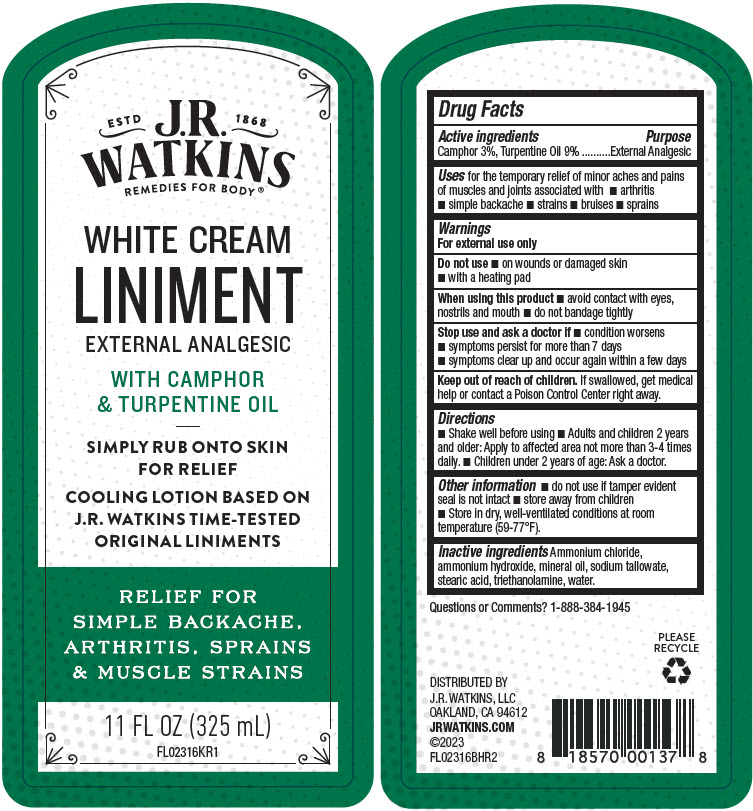 DRUG LABEL: White Cream
NDC: 72342-080 | Form: LINIMENT
Manufacturer: J.R. Watkins, LLC.
Category: otc | Type: HUMAN OTC DRUG LABEL
Date: 20240205

ACTIVE INGREDIENTS: CAMPHOR (NATURAL) 3 g/100 mL; TURPENTINE OIL 9 g/100 mL
INACTIVE INGREDIENTS: WATER; STEARIC ACID; AMMONIUM CHLORIDE; MINERAL OIL; TROLAMINE; AMMONIA; SODIUM TALLOWATE, BEEF

White Cream Liniment

Drug Facts

Active ingredients

Camphor 3%, Turpentine Oil 9%

Purpose

External Analgesic

Uses

for the temporary relief of minor aches and pains of muscles and joints associated with

- arthritis
- simple backache
- strains
- bruises
- sprains

Warnings

For external use only

Do not use

- on wounds or damaged skin
- with a heating pad

When using this product

- avoid contact with eyes, nostrils and mouth
- do not bandage tightly

Stop use and ask a doctor if

- condition worsens
- symptoms persist for more than 7 days
- symptoms clear up and occur again within a few days

Keep out of reach of children.If swallowed, get medical help or contact a Poison Control Center right away.

Directions

- Shake well before using
- Adults and children 2 years and older: Apply to affected area not more than 3-4 times daily.
- Children under 2 years of age: Ask a doctor.

Other information

- do not use if tamper evident seal is not intact
- store away from children
- Store in dry, well-ventilated conditions at room temperature (59-77°F).

Inactive ingredients

Ammonium chloride, ammonium hydroxide, mineral oil, sodium tallowate, stearic acid, triethanolamine, water.

Questions or Comments?

1-888-384-1945

DISTRIBUTED BY
J.R. WATKINS, LLC
OAKLAND, CA 94612

PRINCIPAL DISPLAY PANEL - 325 mL Bottle Label

ESTD
1868

J.R.
WATKINS
REMEDIES FOR BODY®

WHITE CREAM
LINIMENT
EXTERNAL ANALGESIC

WITH CAMPHOR
& TURPENTINE OIL

SIMPLY RUB ONTO SKIN
FOR RELIEF

COOLING LOTION BASED ON
J.R. WATKINS TIME-TESTED
ORIGINAL LINIMENTS

RELIEF FOR
SIMPLE BACKACHE,
ARTHRITIS, SPRAINS
& MUSCLE STRAINS

11 FL OZ (325 mL)

FL02316KR1